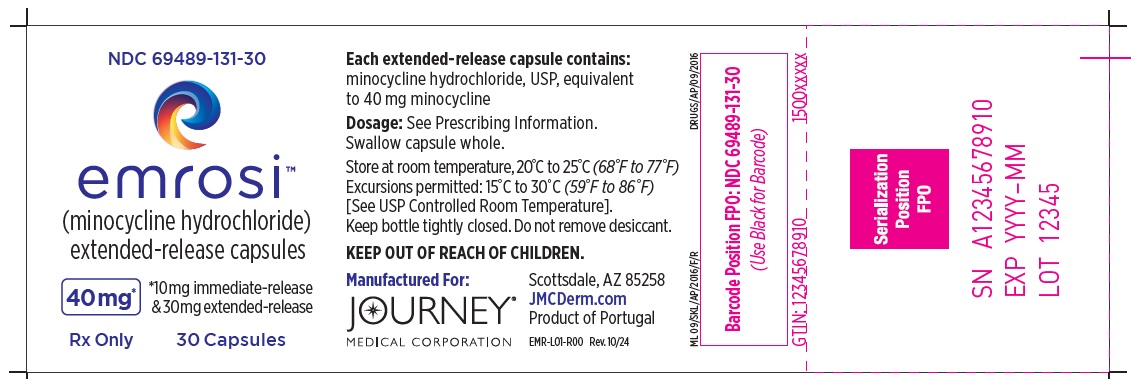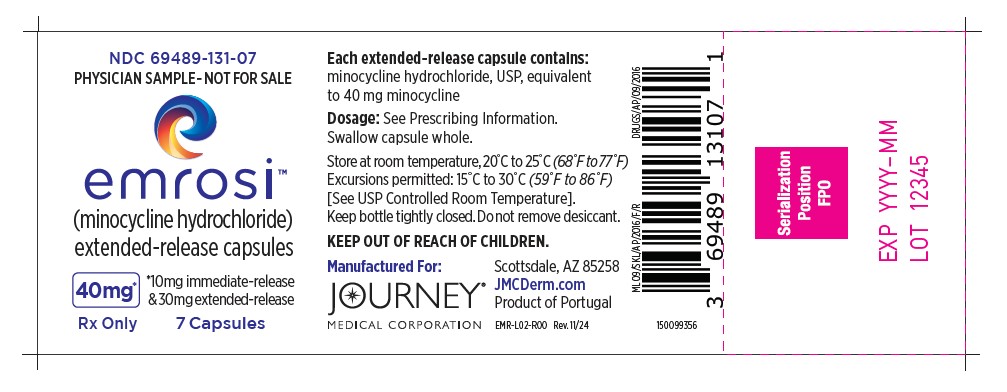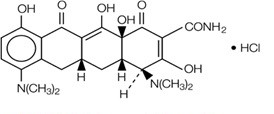 DRUG LABEL: EMROSI
NDC: 69489-131 | Form: CAPSULE
Manufacturer: Journey Medical Corporation
Category: prescription | Type: HUMAN PRESCRIPTION DRUG LABEL
Date: 20250422

ACTIVE INGREDIENTS: MINOCYCLINE HYDROCHLORIDE 40 mg/1 1
INACTIVE INGREDIENTS: ETHYLCELLULOSE, UNSPECIFIED; HYPROMELLOSES; HYDROXYPROPYL CELLULOSE, UNSPECIFIED; MICROCRYSTALLINE CELLULOSE; POLYETHYLENE GLYCOL, UNSPECIFIED; TRIETHYL CITRATE; TALC; GELATIN; FERRIC OXIDE RED; TITANIUM DIOXIDE; PROPYLENE GLYCOL; AMMONIA; SHELLAC

HIGHLIGHTS OF PRESCRIBING INFORMATION

These highlights do not include all the information needed to use EMROSI safely and effectively. See full prescribing information for EMROSI.
EMROSITM (minocycline hydrochloride) extended-release capsules, for oral use
Initial U.S. Approval: 1971

1 INDICATIONS AND USAGE

EMROSI is a tetracycline-class drug indicated to treat inflammatory lesions (papules and pustules) of rosacea in adults. (1)

Limitations of Use

This formulation of minocycline has not been evaluated in the treatment or prevention of infections. To reduce the development of drug-resistant bacteria and to maintain the effectiveness of other antibacterial drugs, use EMROSI only as indicated. (1)

2 DOSAGE AND ADMINISTRATION

The recommended dosage of EMROSI is 40 mg orally, once daily. (2)

3 DOSAGE FORMS AND STRENGTHS

Extended-release capsules: 40 mg. (3)

4 CONTRAINDICATIONS

Known hypersensitivity to any of the tetracyclines. (4)

5 WARNINGS AND PRECAUTIONS

- Serious Skin/Hypersensitivity Reactions:Minocycline has been associated with anaphylaxis, serious skin reactions, erythema multiforme, and drug rash with eosinophilia and systemic symptoms (DRESS) syndrome. Discontinue EMROSI immediately if symptoms occur. (5.1)
- Tooth Discoloration and Enamel Hypoplasia:The use of EMROSI during tooth development (second and third trimesters of pregnancy, infancy, and childhood up to the age of 8 years) may cause permanent discoloration of the teeth (yellow-gray-brown). (5.2)
- Inhibition of Bone Growth:Use during the second and third trimesters of pregnancy, infancy, and childhood up to the age of 8 years may cause reversible inhibition of bone growth. (5.3)
- Clostridioides difficile-Associated Diarrhea (Antibiotic-Associated Colitis): Discontinue if Clostridioides difficile-associated diarrhea (antibiotic-associated colitis) occurs. (5.4)
- Hepatotoxicity:Discontinue EMROSI if liver injury is suspected. (5.5)
- Central Nervous System Effects:May cause central nervous system side effects including light-headedness, dizziness, or vertigo. (5.6)
- Idiopathic Intracranial Hypertension:May cause idiopathic intracranial hypertension in adults and adolescents. Discontinue EMROSI if symptoms occur. (5.7)
- Autoimmune Syndromes:Minocycline has been associated with autoimmune syndromes; discontinue EMROSI immediately if symptoms occur. (5.8)
- Metabolic Effects:If renal impairment exists, monitor serum levels of EMROSI during treatment, discontinue EMROSI if necessary. (5.9)

6 ADVERSE REACTIONS

The most commonly observed adverse reaction (incidence ≥1%) is dyspepsia. (6.1)

To report SUSPECTED ADVERSE REACTIONS, contact Journey Medical Corporation at 1-855-531-1859 or FDA at 1-800-FDA-1088 or www.fda.gov/medwatch.

7 DRUG INTERACTIONS

Patients who are on anticoagulant therapy may require downward adjustment of their anticoagulant dosage. (7.1)

8 USE IN SPECIFIC POPULATIONS

Lactation: Breastfeeding is not recommended. (8.2)

FULL PRESCRIBING INFORMATION

1 INDICATIONS AND USAGE

EMROSI is indicated to treat inflammatory lesions (papules and pustules) of rosacea in adults.

Limitations of Use

- This formulation of minocycline has not been evaluated in the treatment or prevention of infections.
- To reduce the development of drug-resistant bacteria as well as to maintain the effectiveness of other antibacterial drugs, use EMROSI only as indicated.

2 DOSAGE AND ADMINISTRATION

The recommended dosage of EMROSI is one capsule taken orally, once daily. Higher doses have not shown to be of additional benefit in the treatment of rosacea.

EMROSI may be taken with or without food [see Clinical Pharmacology (12.3)] . Ingestion of food along with EMROSI may help to reduce the risk of esophageal irritation and ulceration.

Swallow the capsule whole. Do not crush or chew the extended-release capsule.

3 DOSAGE FORMS AND STRENGTHS

Extended-release capsules: 40 mg.

4 CONTRAINDICATIONS

EMROSI is contraindicated in patients with a history of hypersensitivity to any of the tetracyclines [see Warnings and Precautions (5.1)].

5 WARNINGS AND PRECAUTIONS

5.1 Hypersensitivity Reaction and Serious Skin Reactions

Cases of anaphylaxis, serious skin reactions (e.g., Stevens-Johnson syndrome), erythema multiforme, and drug rash with eosinophilia and systemic symptoms (DRESS) syndrome have been reported postmarketing with minocycline use in patients with acne. DRESS syndrome consists of cutaneous reaction (such as rash or exfoliative dermatitis), eosinophilia, and one or more of the following visceral complications such as: hepatitis, pneumonitis, nephritis, myocarditis, and pericarditis. Fever and lymphadenopathy may be present. In some cases, death has been reported. If this syndrome is recognized, discontinue EMROSI immediately.

5.2 Tooth Discoloration and Enamel Hypoplasia

The use of tetracycline class drugs, including EMROSI during tooth development (second and third trimesters of pregnancy, infancy, and childhood up to the age of 8 years) may cause permanent discoloration of the teeth (yellow-gray-brown). Permanent discoloration of the teeth is more common during long-term use of tetracycline-class drugs but has been observed following repeated short-term courses. Enamel hypoplasia has also been reported. Use of EMROSI is not recommended during tooth development.

Advise the patient of the potential risk to the fetus if EMROSI is used during the second or third trimester of pregnancy [see Use in Specific Populations (8.1, 8.4)].

5.3 Inhibition of Bone Growth

The use of tetracycline-class drugs, including EMROSI, during the second and third trimesters of pregnancy, infancy, and childhood up to the age of 8 years may cause reversible inhibition of bone growth. All tetracyclines, including EMROSI, form a stable calcium complex in any bone-forming tissue. A decrease in fibula growth rate has been observed in premature human infants given oral tetracycline in doses of 25 mg/kg every 6 hours. This reaction was shown to be reversible when the drug was discontinued.

Advise the patient of the potential risk to the fetus if EMROSI is used during the second or third trimester of pregnancy [see Use in Specific Populations (8.1, 8.4)].

5.4 Clostridioides difficile-Associated Diarrhea (Antibiotic-Associated Colitis)

Clostridium difficileassociated diarrhea (CDAD) has been reported with nearly all antibacterial agents, including minocycline, and may range in severity from mild diarrhea to fatal colitis.

C. difficileproduces toxins A and B which contribute to the development of CDAD. Hypertoxin producing strains of C. difficilecause increased morbidity and mortality, as these infections can be refractory to antimicrobial therapy and may require colectomy. CDAD must be considered in all patients who present with diarrhea following antibiotic use. Careful medical history is necessary since CDAD has been reported to occur over two months after the administration of antibacterial agents.

If CDAD is suspected or confirmed, discontinue EMROSI.

5.5 Hepatotoxicity

Postmarketing cases of serious liver injury, including irreversible drug-induced hepatitis and fulminant hepatic failure (sometimes fatal) have been reported with minocycline use in the treatment of acne. Discontinue EMROSI if liver injury is suspected.

5.6 Central Nervous System Effects

Central nervous system side effects including light-headedness, dizziness or vertigo have been reported with minocycline therapy. Caution patients who experience these symptoms about driving vehicles or using hazardous machinery while on EMROSI. These symptoms may disappear during therapy and usually rapidly disappear when the drug is discontinued.

5.7 Idiopathic Intracranial Hypertension

Idiopathic Intracranial hypertension has been associated with the use of tetracyclines. Clinical manifestations of idiopathic intracranial hypertension include headache, blurred vision, diplopia, and vision loss; papilledema can be found on fundoscopy. Women of childbearing age who are overweight or have a history of idiopathic intracranial hypertension are at a greater risk for developing idiopathic intracranial hypertension. Avoid concomitant use of isotretinoin and EMROSI because isotretinoin, a systemic retinoid, is also known to cause idiopathic intracranial hypertension.

Permanent visual loss may exist, even after the medication is discontinued. If visual disturbance occurs during treatment, prompt ophthalmologic evaluation is warranted. Because intracranial pressure can remain elevated for weeks after drug cessation, monitor patients until they stabilize.

5.8 Autoimmune Syndromes

Tetracyclines have been associated with the development of autoimmune syndromes. The long-term use of minocycline in the treatment of acne has been associated with drug-induced lupus-like syndrome, autoimmune hepatitis and vasculitis. Sporadic cases of serum sickness have presented shortly after minocycline use. Symptoms may be manifested by fever, rash, arthralgia, and malaise. Evaluate symptomatic patients. If symptoms occur, immediately discontinue EMROSI.

5.9 Metabolic Effects

The anti-anabolic action of the tetracyclines, including EMROSI, may cause an increase in blood urea nitrogen (BUN). In patients with significantly impaired renal function, higher serum levels of EMROSI may lead to azotemia, hyperphosphatemia, and acidosis. If renal impairment exists, monitor serum levels of EMROSI during treatment, and discontinue EMROSI if necessary.

5.10 Photosensitivity

Photosensitivity manifested by an exaggerated sunburn reaction has been observed in some individuals taking tetracyclines, including minocycline. Advise patients to minimize or avoid exposure to natural or artificial sunlight (tanning beds or UVA/B treatment) while using EMROSI. Instruct patients to use sunscreen products and wear protective apparel (e.g., hat) when exposure to sun cannot be avoided.

5.11 Tissue Hyperpigmentation

Tetracycline-class antibiotics are known to cause hyperpigmentation. EMROSI may induce hyperpigmentation in many organs, including nails, bone, skin, eyes, thyroid, visceral tissue, oral cavity (teeth, mucosa, alveolar bone), sclerae and heart valves. Skin and oral pigmentation has been reported to occur independently of time or amount of drug administration, whereas other tissue pigmentation has been reported to occur upon prolonged administration. Skin pigmentation includes diffuse pigmentation as well as over sites of scars or injury.

5.12 Development of Drug-Resistant Bacteria

Bacterial resistance to the tetracyclines may develop in patients using EMROSI, Because of the potential for drug-resistant bacteria to develop during the use of EMROSI, use EMROSI only as indicated.

5.13 Superinfection

Use of EMROSI may result in overgrowth of nonsusceptible organisms, including fungi. If superinfection occurs, discontinue EMROSI and institute appropriate therapy.

5.14 Laboratory Monitoring

Perform periodic laboratory evaluations of organ systems, including hematopoietic, renal and hepatic studies.

6 ADVERSE REACTIONS

The following clinically significant adverse reactions are described elsewhere in the labeling:

- Serious Skin/Hypersensitivity Reactions [see Warnings and Precautions (5.1)]
- Clostridioides difficile-Associated Diarrhea (Antibiotic-Associated Colitis) [see Warnings and Precautions (5.4)]
- Hepatotoxicity [see Warnings and Precautions (5.5)]
- Central Nervous System Effects [see Warnings and Precautions (5.6)]
- Idiopathic Intracranial Hypertension [see Warnings and Precautions (5.7)]

6.1 Clinical Trials Experience

Because clinical trials are conducted under widely varying conditions, adverse reaction rates observed in the clinical trials of a drug cannot be directly compared to rates in the clinical trials of another drug and may not reflect the rates observed in practice.

In two clinical trials, MVOR-1 and MVOR-2, a total of 638 adult subjects were analyzed under the safety population with 243 subjects in EMROSI group, 237 subjects in doxycycline (40 mg) group and 158 subjects in placebo group [see Clinical Studies (14)].

The most common adverse reaction reported by ≥1% of subjects treated with EMROSI and more frequently than in subjects receiving placebo was dyspepsia, which was reported in 2% of subjects treated with EMROSI and none of the subjects receiving placebo.

6.2 Postmarketing Experience

The following adverse reactions have been reported with post-approval use of minocycline hydrochloride in a variety of indications. Because these reactions are reported voluntarily from a population of uncertain size, it is not always possible to reliably estimate their frequency or establish a causal relationship to drug exposure.

Skin and hypersensitivity reactions:anaphylaxis, angioedema, DRESS syndrome, erythema multiforme, Stevens-Johnson syndrome, acute febrile neutrophilic dermatosis (Sweet’s syndrome), fixed drug eruptions, balanitis, anaphylactoid purpura photosensitivity, pigmentation of skin and mucous membranes.

Autoimmune conditions:polyarthralgia, pericarditis, exacerbation of systemic lupus, pulmonary infiltrates with eosinophilia, lupus-like syndrome.

Central nervous system:idiopathic intracranial hypertension, bulging fontanels in infants, decreased hearing.

Endocrine:brown-black microscopic thyroid discoloration, abnormal thyroid function.

Oncology:thyroid cancer.

Oral:glossitis, dysphagia, tooth discoloration.

Gastrointestinal:enterocolitis, pancreatitis, hepatitis, liver failure.

Renal:acute renal failure.

Hematology:hemolytic anemia, thrombocytopenia, eosinophilia.

7 DRUG INTERACTIONS

7.1 Anticoagulants

Because tetracyclines have been shown to decrease plasma prothrombin activity, patients who are on anticoagulant therapy may require downward adjustment of their anticoagulant dosage.

7.2 Penicillin

Because bacteriostatic drugs may interfere with the bactericidal action of penicillin, avoid giving EMROSI in conjunction with penicillin.

7.3 Antacids and Iron Preparations

Absorption of tetracyclines is impaired by antacids containing aluminum, calcium or magnesium and iron-containing preparations.

7.4 Drug/Laboratory Test Interactions

False elevations of urinary catecholamine levels may occur due to interference with the fluorescence test.

8 USE IN SPECIFIC POPULATIONS

8.1 Pregnancy

Risk Summary

Tetracycline-class drugs, including EMROSI, may cause permanent discoloration of deciduous teeth and reversible inhibition of bone growth when administered during the second and third trimesters of pregnancy [see Warnings and Precautions (5.2, 5.3) and Use in Specific Populations (8.4)]. A few postmarketing cases of limb reductions have been reported over decades of use; however, the association is unclear. The limited data from postmarketing reports are not sufficient to inform a drug-associated risk for birth defects or miscarriage.

In animal reproduction studies conducted in pregnant rats and rabbits, bent limb bones were observed following oral administration of minocycline hydrochloride during organogenesis at systemic exposure of approximately 7.1 and 4.8 times, respectively, the maximum recommended human dose (MRHD) based on AUC exposures (see Data).

If the patient becomes pregnant while taking this drug, advise the patient of the risk to the fetus and discontinue treatment.

The background risk of major birth defects and miscarriage for the indicated population is unknown. All pregnancies have a background risk of birth defect, loss, or other adverse outcomes. In the U.S. general population, the estimated background risk of major birth defects and miscarriage in clinically recognized pregnancies is 2 to 4% and 15 to 20%, respectively.

Data

Human Data

The use of tetracycline class drugs, including EMROSI, during tooth development (second and third trimesters of pregnancy, infancy, and childhood up to the age of 8 years) may cause permanent discoloration of deciduous teeth (yellow-gray-brown). Permanent discoloration of the teeth is more common during long-term use of the drug but has been observed following repeated short-term courses [see Warnings and Precautions (5.2)].

Animal Data

Results of animal studies indicate that minocycline hydrochloride crosses the placenta, are found in fetal tissues, and can cause delayed skeletal development in the developing fetus. Evidence of embryotoxicity has been noted in animals treated early in pregnancy [see Warnings and Precautions (5.3)].

Minocycline hydrochloride induced skeletal malformations (bent limb bones) in fetuses when administered to pregnant rats and rabbits during the period of organogenesis at doses of 30 mg/kg/day and 100 mg/kg/day, respectively, (7.1 and 4.8 times, respectively, the MRHD based on AUC comparison). Reduced mean fetal body weight was observed in studies in which minocycline hydrochloride was administered to pregnant rats at an oral dose of 10 mg/kg/day (2.4 times the MRHD based on AUC comparison).

Minocycline hydrochloride was assessed for effects on peri- and post-natal development of rats in a study that involved oral administration to pregnant rats during the period of organogenesis through lactation at doses of 5, 10, or 50 mg/kg/day. In this study, body weight gain was significantly reduced in pregnant females that received 50 mg/kg/day (6 times the MRHD based on AUC comparison). No effects of treatment on the duration of the gestation period or the number of live pups born per litter were observed. Gross external anomalies observed in offspring of animals that received minocycline hydrochloride at 50 mg/kg/day included reduced body size, improperly rotated forelimbs, and reduced size of extremities. No effects were observed on the physical development, behavior, learning ability, or reproduction of the offspring of animals that received minocycline hydrochloride.

8.2 Lactation

Risk Summary

Tetracycline-class antibiotics, including minocycline, are present in breast milk following oral administration. There are no data on the effects of minocycline on milk production. Because of the potential for serious adverse reactions, including tooth discoloration and inhibition of bone growth, advise patients that breastfeeding is not recommended during EMROSI therapy and for 4 days after the final dose [see Warnings and Precautions (5.2, 5.3)].

8.4 Pediatric Use

The safety and effectiveness of EMROSI have not been established in pediatric patients.

Tooth discoloration and inhibition of bone growth have been observed in pediatric patients with the use of tetracycline class antibiotics [see Warnings and Precaution (5.2, 5.3)].

8.5 Geriatric Use

Of the 653 subjects in the phase 3 clinical trials of EMROSI, 101 (15.5%) subjects were 65 years of age and older and 25 (3.8%) were 75 years of age and older. No overall differences in safety or effectiveness of EMROSI have been observed between subjects 65 years of age and older and younger adult subjects.

10 OVERDOSAGE

Minocycline is not removed in significant quantities by hemodialysis or peritoneal dialysis. In case of overdosage, discontinue EMROSI, treat symptomatically and institute supportive measures. Call Poison Control Center at 1-800-222-1222 for the latest recommendations.

11 DESCRIPTION

Minocycline hydrochloride, a semi synthetic derivative of tetracycline, is [4S-(4α,4aα,5aα,12aα)]-4,7-Bis(dimethylamino)-1,4,4a,5,5a,6,11,12a-octahydro-3,10,12,12a- tetrahydroxy-1,11-dioxo-2-naphthacenecarboxamide mono hydrochloride. Its molecular formula is C23H27N3O7•HCl with a molecular weight of 493.95. Minocycline hydrochloride has the following structure:

Minocycline hydrochloride is a yellow, hygroscopic, crystalline powder. It is sparingly soluble in water, slightly soluble in ethanol (96%). A 1% w/v solution in water has pH between 3.5 and 4.5.

Each EMROSI extended-release capsule contains 40 mg of minocycline (equivalent to 43.19 mg of minocycline hydrochloride) as 10 mg immediate-release and 30 mg extended-release beads and the following inactive ingredients: ethyl cellulose, hypromellose, isopropyl alcohol, microcrystalline cellulose, Opadry®clear, polyethylene glycol 400, triethyl citrate and talc. Opadry®clear contains: hydroxypropyl cellulose and hypromellose. Capsule shell contains gelatin, iron oxide red and titanium dioxide. White ink contains ammonia, butyl alcohol, dehydrated alcohol, isopropyl alcohol, potassium hydroxide, propylene glycol, titanium dioxide and shellac.

12 CLINICAL PHARMACOLOGY

12.1 Mechanism of Action

The mechanism of action of EMROSI for the treatment of rosacea is unknown.

12.2 Pharmacodynamics

The pharmacodynamics of EMROSI for the treatment of rosacea are unknown.

12.3 Pharmacokinetics

EMROSI is not bioequivalent to any other minocycline products. The pharmacokinetics of minocycline following administration of EMROSI was investigated in two studies that enrolled 32 healthy, adult subjects. In Study 1, the plasma pharmacokinetic parameters for EMROSI following single dose administration under fasting and fed states are presented in Table 1.

Table 1: Plasma Pharmacokinetic Parameters [Mean (%CV)] for EMROSI (40 mg)

 | N | Cmax; (ng/mL) | Tmax* (hr) | AUCinf (ng.hr/mL) | t1/2 (hr)
EMROSI (Fasting) | 23 | 243.9 (37.3) | 1.50 (1.00 – 4.17) | 3933.6 (31.2) | 14.67 (26.7)
EMROSI (Fed) | 23 | 225.0 (16.7) | 4.50 (3.00 – 8.00) | 4404.1 (21.0) | 14.93 (21.5)

Note: * Median (Range)

In Study 2, minocycline plasma PK following EMROSI single (Day 1) and after repeated (Day 21) once daily administrations in eight (8) subjects were found to be similar with overlapping ranges. The mean Cmaxwas 382.83 ng/mL versus 337.74 ng/mL and AUC0-24was 3549.64 ng*hr/mL versus 3957.62 ng*hr/mL, respectively on Day 1 versus Day 21.

Absorption:In Study 1, the median plasma Tmaxof minocycline from EMROSI was 1.50 hours (1.00 - 4.17). In Study 2, the median plasma Tmaxvalues of minocycline from EMROSI on Day 1 and Day 21 were 1.75 and 1.5 hours, respectively.

Effect of Food:Following administration of EMROSI with a high-fat meal (1011 Kcal, 53% fat), Tmaxwas delayed by approximately 3 hours. The high fat meal did not impact the Cmaxhowever, the AUCinfwas increased by 15.26% (Table 1) [see Dosage and Administration (2)].

Distribution:Minocycline is lipid soluble and distributes into the skin and sebum. In Study 1, the mean apparent volume of distribution (Vz/F) values of minocycline following oral administration of EMROSI at fasting and fed condition were 229.61 (±67.83) L and 199.83 (±43.71) L, respectively.

Elimination:The mean apparent elimination half-life (t½) of minocycline from EMROSI was approximately 15 hours independent of fasting and fed dosing condition.

13 NONCLINICAL TOXICOLOGY

13.1 Carcinogenesis, Mutagenesis, Impairment of Fertility

In an oral carcinogenicity study in rats in which minocycline hydrochloride was administered once daily for up to 104 weeks at doses up to 200 mg/kg/day, minocycline hydrochloride increased incidences of follicular cell tumors of the thyroid gland in both sexes, including adenomas, carcinomas, and the combined incidence of adenomas and carcinomas in males and adenomas and the combined incidence of adenomas and carcinomas in females. In an oral carcinogenicity study in mice in which minocycline hydrochloride was administered once daily for up to 104 weeks at doses up to 150 mg/kg/day, minocycline hydrochloride did not increase tumor incidence.

Minocycline hydrochloride was not mutagenic in vitro in a bacterial reverse mutation assay (Ames test) or CHO/HGPRT mammalian cell assay in the presence or absence of metabolic activation. Minocycline hydrochloride was not clastogenic in vitrousing human peripheral blood lymphocytes or in vivoin a mouse micronucleus test.

Male and female reproductive performance in rats was unaffected by oral doses of minocycline hydrochloride up to 300 mg/kg/day (95 times the MRHD based on AUC comparison). However, doses of 100 mg/kg/day (36 times the MRHD based on AUC comparison) and higher to male rats adversely affected spermatogenesis. At 100 mg/kg/day, minocycline increased morphological abnormalities, including absent heads, misshapen heads, and abnormal flagella. At 300 mg/kg/day, minocycline also reduced the number of sperm cells per gram of epididymis and reduced the percentage of motile sperm.

14 CLINICAL STUDIES

The safety and efficacy of EMROSI in the treatment of inflammatory lesions and erythema of rosacea was assessed in two 16-week, multi-center, randomized, double-blind, active- and placebo-controlled trials (MVOR-1 [NCT05296629] and MVOR-2 [NCT05343455]) in adults. In the two trials, a total of 653 subjects with papulopustular rosacea received EMROSI or doxycycline capsules 40 mg or placebo for up to 16 weeks.

Subjects were required to have an inflammatory lesion count (papules and pustules) in the range 15-60 lesions and an Investigator’s Global Assessment (IGA) score of 3 (“moderate”) or 4 (“severe”) at baseline.

The mean age of subjects was 49 years and subjects were from the following racial groups: White (93%), Asian (4%), Black or African American (2%), and Other (1%); for ethnicity, 38% of subjects identified as Hispanic or Latino. At baseline, subjects had a mean inflammatory lesion count of 25 (ranged 15 to 58), 88% were scored as moderate (IGA=3), and 12% were scored as severe (IGA=4).

The co-primary efficacy endpoints were the proportion of subjects with IGA ‛treatment success’ at Week 16 (defined as an IGA score of 0 [“clear”] or 1 [“near clear”] with at least a 2-grade reduction from baseline) and the absolute change from baseline in total inflammatory lesion counts at Week 16, in the EMROSI group compared to the placebo group. The efficacy results are presented in Table 2.

Table 2: Efficacy Results at Week 16 in Trials MVOR-1 and MVOR-2

Endpoint | Trial MVOR-1 |  |  | Trial MVOR-2
Endpoint | EMROSI; (N=122) | Doxycycline; (N=121) | Placebo; (N=80) | EMROSI; (N=123) | Doxycycline; (N=125) | Placebo; (N=82)
IGA Treatment; Success^1 | 65% | 46% | 31% | 60% | 31% | 27%
Difference from; Placebo (95% CI) | 33% (20%, 46%) |  |  | 34% (21%, 47%)
Difference from; Doxycycline (95% CI) | 18% (5%, 31%) |  |  | 28% (17%, 39%)
Inflammatory Lesion Counts
Mean^2Absolute Change from Baseline | -20.6 | -15.6 | -11.4 | -18.1 | -14.6 | -11.2
Difference from; Placebo (95% CI) | -9.3 (-11.6, -6.9) |  |  | -6.9 (-9.1, -4.6)
Difference from; Doxycycline (95% CI) | -5.1 (-7.2, -2.9) |  |  | -3.4 (-5.4, -1.5)
Mean^2 Percent Change from Baseline | -79% | -63% | -47% | -75% | -60% | -46%
Difference from; Placebo (95% CI) | -33% (-41%, -24%) |  |  | -30% (-39%, -20%)
Difference from; Doxycycline (95% CI) | -16% (-24%, -8%) |  |  | -15% (-23%, -7%)

^1Investigator’s Global Assessment (IGA) treatment success was defined as an IGA score of 0 or 1 with at least a 2-grade reduction from baseline.

^2Means presented in table are Least Square (LS) means.

16 HOW SUPPLIED/STORAGE AND HANDLING

How Supplied

EMROSI is an opaque, brownish-red colored, hard gelatin capsule, imprinted “MEC” on both cap and body with white ink.

Bottles of 30 capsules with child-resistant closure, NDC 69489-131-30.

Storage and Handling

Store at room temperature 20°C to 25°C (68°F to 77°F); excursions are permitted to 15ºC to 30ºC (59ºF to 86ºF) [see USP Controlled Room Temperature].

Protect from light, moisture, and excessive heat.

17 PATIENT COUNSELING INFORMATION

Advise the patient to read the FDA-approved patient labeling (Patient Information).

Advise patients taking EMROSI extended-release capsules of the following information and instructions:

Administration Instructions

- EMROSI should be taken exactly as directed.
- Advise patients to swallow EMROSI capsule whole and not to chew or crush the capsule [see Dosage and Administration (2)].

Serious Skin/Hypersensitivity Reactions

- Inform patients that serious skin reactions have occurred with minocycline use in patients with acne. Advise patients to discontinue use of EMROSI and contact their healthcare provider immediately at the first evidence of skin erythema [see Warnings and Precautions (5.1)].

Tooth Discoloration and Enamel Hypoplasia

- Advise patients that EMROSI use in pregnancy may cause permanent tooth discoloration of deciduous teeth. Advise patients to discontinue EMROSI during pregnancy and to inform their healthcare provider right away if they become pregnant during treatment [see Warnings and Precautions (5.2), Use in Specific Populations (8.1)].

Inhibition of Bone Growth

- Advise patients that EMROSI use in pregnancy may cause inhibition of fetal bone growth. Advise patients to discontinue EMROSI during pregnancy and to inform their healthcare provider right away if they become pregnant during treatment [see Warnings and Precautions (5.3), Use in Specific Populations (8.1)].

Clostridioides difficile-Associated Diarrhea (Antibiotic-Associated Colitis)

- Advise patients that Clostridioides difficile-associated diarrhea (antibiotic-associated colitis) can occur with minocycline therapy, including EMROSI. If patients develop watery or bloody stools, advise patients to seek medical attention [see Warnings and Precautions (5.4)].

Hepatotoxicity

- Inform patients about the possibility of hepatotoxicity. Advise patients to seek medical advice if they experience signs or symptoms of hepatotoxicity, including loss of appetite, tiredness, diarrhea, jaundice, bleeding easily, confusion, and sleepiness [see Warnings and Precautions (5.5)].

Central Nervous System Effects

- Inform patients that central nervous system adverse reactions including dizziness or vertigo have been reported with oral minocycline therapy. Caution patients about driving vehicles or using hazardous machinery if they experience such symptoms while on EMROSI [see Warnings and Precautions (5.6)].

Idiopathic Intracranial Hypertension

- Inform patients that idiopathic intracranial hypertension can occur with minocycline therapy. Advise patients to seek medical attention if they develop unusual headache, visual symptoms, such as blurred vision, diplopia, and vision loss [see Warnings and Precautions (5.7)].

Autoimmune Syndromes

- Inform patients that autoimmune syndromes, including drug-induced lupus-like syndrome, autoimmune hepatitis, vasculitis, and serum sickness have been observed with tetracycline-class drugs, including minocycline. Symptoms may be manifested by arthralgia, fever, rash, and malaise. Advise patients who experience such symptoms to immediately discontinue EMROSI and seek medical help [see Warnings and Precautions (5.8)].

Photosensitivity

- Inform patients that photosensitivity manifested by an exaggerated sunburn reaction has been observed in some individuals taking tetracyclines, including minocycline. Advise patients to minimize or avoid exposure to natural or artificial sunlight (i.e., tanning beds or UVA/B treatment) while using EMROSI. Instruct patients to use sunscreen and wear protective clothing (e.g., hat) over treated areas when exposure to sun cannot be avoided [see Warnings and Precautions (5.10)].

Tissue Hyperpigmentation

- Inform patients that EMROSI may cause discoloration of skin, scars, teeth, or gums [see Warnings and Precautions (5.11)] .

Lactation

- Advise patients that EMROSI therapy is not recommended during breast feeding for 4 days after the final dose [see Use in Specific Populations (8.2)].

Manufactured for:

Journey Medical Corporation
Scottsdale, AZ 85258

EMR-P01-R01

EMROSI is a trademark of Journey Medical Corporation.

All other trademarks are the properties of their respective owners. Copyright © 2024, Journey Medical Corporation. All rights reserved.

PATIENT INFORMATION

EMROSITM(em-ROH-see)

(minocycline hydrochloride)

extended-release capsules, for oral use

What is EMROSI?

EMROSI is a prescription medicine used to treat adults with pimples and bumps (inflammatory lesions) caused by a condition called rosacea.

It is not known if EMROSI is:

- safe and effective for the treatment of infections
- safe and effective in children under the age of 18 years

Who should not take EMROSI?

Do not take EMROSIif you are allergic to any tetracycline medicines. Ask your healthcare provider or pharmacist for a list of these medicines if you are not sure.

Before taking EMROSI, tell your healthcare provider about all of your medical conditions, including if you:

- have diarrhea or watery stools
- have liver problems
- have kidney problems
- have had increased pressure around your brain that may have cause vision problems
- are pregnant or plan to become pregnant. EMROSI may harm your unborn baby. Taking EMROSI while you are pregnant may cause serious side effects on the growth of bone and teeth of your baby. Stop taking EMROSI and call your healthcare provider right away if you become pregnant during treatment with EMROSI
- are breastfeeding or plan to breastfeed. EMROSI passes into your milk and may harm your baby. Do not breastfeed during treatment with EMROSI and for 4 days after your final dose

Tell your healthcare provider about all the other medicines you take,including prescription and over-the counter medicines, vitamins and herbal supplements.

EMROSI and other medicines may affect each other and cause serious side effects. EMROSI may affect the way other medicines work, and other medicines may affect how EMROSI works.

Especially tell your healthcare provider if you take:

- a blood thinner medicine
- penicillin antibiotic medicine
- antacids that contain aluminum, calcium, or magnesium or iron-containing medicines
- an acne medicine that contains isotretinoin

Ask your healthcare provider or pharmacist if you are not sure if your medicine is one that is listed above. Know the medicines you take. Keep a list of them to show your healthcare provider and pharmacist.

How should I take EMROSI?

- Take EMROSI exactly as your healthcare provider tells you
- Take EMROSI 1 time per day with or without food. Taking EMROSI with food may lower your chances of getting irritation or ulcers in your esophagus. Your esophagus is the tube that connects your mouth to your stomach
- Swallow EMROSI whole. Do not chew or crush the capsules

If you take too much EMROSI, call your healthcare provider or Poison Help line at 1-800-222-1222 or go to the nearest hospital emergency room right away.

What should I avoid while taking EMROSI?

- You should not drive or operate dangerous machinery until you know how EMROSI affects you. EMROSI may cause you to feel dizzy or lightheaded or have a spinning feeling (vertigo)
- Avoid sunlight or artificial sunlight, such as sunlamps and tanning beds during treatment with EMROSI. EMROSI can make your skin sensitive to the sun and artificial sunlight and you could get severe sunburn during treatment. Use sunscreen and wear a hat and protective clothing that covers your skin while out in the sunlight during treatment with EMROSI

What are the possible side effects of EMROSI?

EMROSI may cause serious side effects, including:

- Serious skin and allergic reactionshave happened during treatment with minocycline. EMROSI may cause serious skin or allergic reactions that may also affect parts of your body such as your liver, lungs, kidneys, and heart. Sometimes these reactions can lead to death. Stop taking EMROSI and call your healthcare provider right away or go to the nearest hospital emergency room if you have any of the following signs or symptoms, including:
  - skin redness, rash, hives, sores in your mouth, or your skin blisters and peels
  - swelling of your face, eyes, lips, tongue, or throat
  - trouble swallowing or breathing
  - blood in your urine
  - fever, yellowing of the skin or the whites of your eyes (jaundice), dark colored urine
  - pain on the right side of the stomach area (abdominal pain)
  - chest pain or abnormal heartbeats
  - swelling in your legs, ankles, and feet
- Permanent tooth discoloration and problems with tooth enamel.EMROSI may permanently turn a baby or child's teeth yellow-grey-brown during tooth development. EMROSI may cause tooth enamel to not develop properly. You should not use EMROSI during tooth development. Tooth development happens in the second and third trimesters of pregnancy, and in children from birth to 8 years of age. See “Before taking EMROSI, tell your healthcare provider about all your medical conditions, including if you:”
- Slow bone growth.EMROSI may cause slow bone growth if it is used during the second and third trimesters of pregnancy and if it is used in infants and children up to 8 years of age. Slow bone growth is reversible after stopping treatment with EMROSI.
- Diarrhea (antibiotic associated colitis).Antibiotic associated colitis can happen with most antibiotics, including EMROSI. This type of diarrhea may be caused by an infection (Clostridioides difficile) in your intestines and can be severe and lead to death. Call your healthcare provider right away if you get watery diarrhea, diarrhea that does not go away, or bloody stools.
- Liver problems.EMROSI may cause serious liver problems that can lead to death.Stop taking EMROSI and call your healthcare provider right away if you get any of the following symptoms of liver problems:
  - loss of appetite
  - tiredness
  - diarrhea
  - yellowing of your skin or the whites of your eyes
  - unexplained bleeding or bleeding easily than normal
  - confusion
  - sleepiness

- Central nervous system effects.See “ What should I avoid while taking EMROSI?” Central nervous system effects such as light headedness, dizziness, and a spinning feeling (vertigo) may go away during your treatment with EMROSI or if treatment is stopped.
- Increased pressure around the brain (idiopathic intracranial hypertension).This condition may lead to vision changes and permanent vision loss. You are more likely to get intracranial hypertension if you are a female who can have children, are overweight, and have already had intracranial hypertension. Stop taking EMROSI and tell your healthcare provider right away if you have unusual headaches, blurred vision, double vision, and vision loss.
- Immune system reactions including a lupus-like syndrome, hepatitis, and inflammation of blood or lymph vessels (vasculitis).Using EMROSI for a long time to treat acne may cause immune system reactions. Stop taking EMROSI and tell your healthcare provider right away if you get a fever, rash, joint pain, or body weakness.
- Sensitivity to sunlight (photosensitivity).See “ What should I avoid while taking EMROSI?”
- Discoloration (tissue hyperpigmentation).EMROSI may cause darkening of your nails, bone, skin, eyes, teeth, gums, scars, and internal organs.

The most common side effects of EMROSI includestomach upset or burning (dyspepsia) after eating or drinking.

Your healthcare provider may do blood tests and check you for side effects during treatment with EMROSI and may stop treatment if you develop certain side effects.

These are not all the side effects with EMROSI.

Call your doctor for medical advice about side effects. You may report side effects to FDA at 1-800-FDA-1088.

You may also report side effects to Journey Medical Corporation at 1-855-531-1859.

How should I store EMROSI?

- Store EMROSI at room temperature between 68°F to 77°F (20°C to 25°C)
- EMROSI comes in a child-resistant package
- Keep EMROSI container tightly closed
- Keep EMROSI away from light, moisture, and excessive heat
- Do not eat desiccant

Keep EMROSI out of the reach of children

General information about the safe and effective use of EMROSI.
Medicines are sometimes prescribed for purposes other than those listed in the Patient Information leaflet. Do not use EMROSI for a condition for which it was not prescribed. Do not give EMROSI to other people, even if they have the same symptoms you have. It may harm them. You can ask your pharmacist or healthcare provider for information about EMROSI that is written for health professionals.

What are the ingredients in EMROSI?

Active ingredient:minocycline hydrochloride

Inactive ingredients:ethyl cellulose, hypromellose, isopropyl alcohol, microcrystalline cellulose, Opadry clear, polyethylene glycol, triethyl citrate, and talc

Manufactured for:

Journey Medical Corporation

Scottsdale, AZ 85258

For more information, go to www.journeymedicalcorp.comor call 1-855-531-1859

This Patient Information has been approved by the U.S. Food and Drug Administration. Revised: 11/2024

EMR-P02-R01

EMROSI is a trademark of Journey Medical Corporation.

All other trademarks are the properties of their respective owners.

Copyright © 2024, Journey Medical Corporation. All rights reserved.

PACKAGE LABEL

PRINCIPAL DISPLAY PANEL

NDC 69489-131-30

emrosiTM

(minocycline hydrochloride)

extended-release capsules

40mg*

*10mg immediate-release
& 30mg extended-release

Rx Only

30 Capsules

PRINCIPAL DISPLAY PANEL

NDC 69489-131-07

PHYSICIAN SAMPLE-NOT FOR SALE

emrosiTM

(minocycline hydrochloride)

extended-release capsules

40mg*

*10mg immediate-release
& 30mg extended-release

Rx Only

7 Capsules